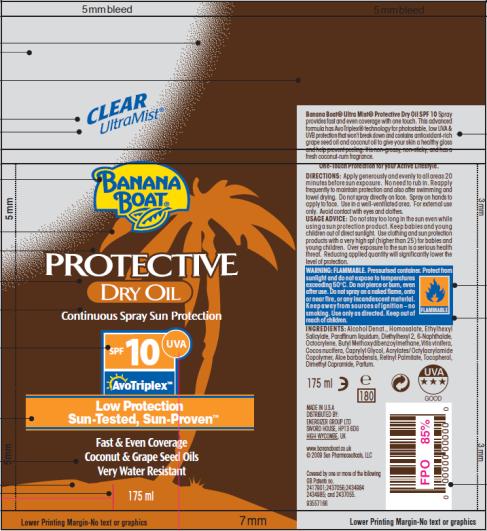 DRUG LABEL: Banana Boat Protective Dry SPF 10
NDC: 17630-2012 | Form: OIL
Manufacturer: Accra-Pac, Inc.
Category: otc | Type: HUMAN OTC DRUG LABEL
Date: 20100325

ACTIVE INGREDIENTS: HOMOSALATE 0.06 mL/1 mL; OCTISALATE 0.06 mL/1 mL; OCTOCRYLENE 0.025 mL/1 mL; AVOBENZONE 0.015 mL/1 mL
INACTIVE INGREDIENTS: MINERAL OIL; CAPRYLYL GLYCOL; VITAMIN A PALMITATE; GRAPE SEED OIL; COCONUT OIL; ALOE VERA LEAF

Banana Boat Protective Dry Oil SPF 10

Active Ingredients:

Homosalate 0.06mL / 1mL

Octisalate 0.06mL / 1mL

Octocrylene 0.025mL / 1mL

Avobenzone 0.015mL / 1mL

DIRECTIONS:

Apply generously and evenly to all areas 20 minutes before sun exposure. No need to rub in. Reapply frequently to maintain protection and also after swimming and towel drying. Do not spray directly on face. Spray on hands to apply to face. Use in a well-ventilated area. For external use only. Avoid contact with eyes and clothes.

USAGE ADVICE:

Do not stay too long in the sun even while using a sun protection product. Keep babies and young children out of direct sunlight. Use clothing and sun protection products with a very high SPF (higher than 25) for babies and young children. Over exposure to the sun is a serious health threat. Reducing applied quantity will significantly lower the level of protection.

WARNING:

FLAMMABLE. Pressurized container. Protect from sunlight and do not expose to temperatures exceeding 50ºC. Do not pierce or burn, even after use. Do not spray on a naked flame, onto or near fire, or any incandescent material. Keep away from sources of ignition – no smoking. Use only as directed. Keep out of reach of children.

INGREDIENTS:

Alcohol Denat., Homosalate, Ethylhexyl Salicylate, Paraffinum liquidum, Diethylhexyl 2, 6-Naphthalate, Octocrylene, Butyl Methoxydibenzoylmethane,Vitis vinifera, Cocos nucifera, Caprylyl Glycol, Acrylates/ Octylacrylamide Copolymer, Aloe barbadensis, Retinyl Palmitate, Tocopherol, Dimethyl Capramide, Parfum.

FLAMMABLE
MADE IN U.S.A
DISTRIBUTED BY:
ENERGIZER GROUP LTD
SWORD HOUSE, HP13 6DG
HIGH WYCOMBE, UK
www.bananaboat.co.uk

PRINCIPAL DISPLAY PANEL

CLEAR
UltraMist®
BANANA
BOAT®
PROTECTIVE
DRY OIL
Continuous Spray Sun Protection
SPF 10 UVA
AvoTriplex TM
Low Protection
Sun-Tested, Sun-Proven TM
Fast & Even Coverage
Coconut & Grape Seed Oils
Very Water Resistant
175 ml